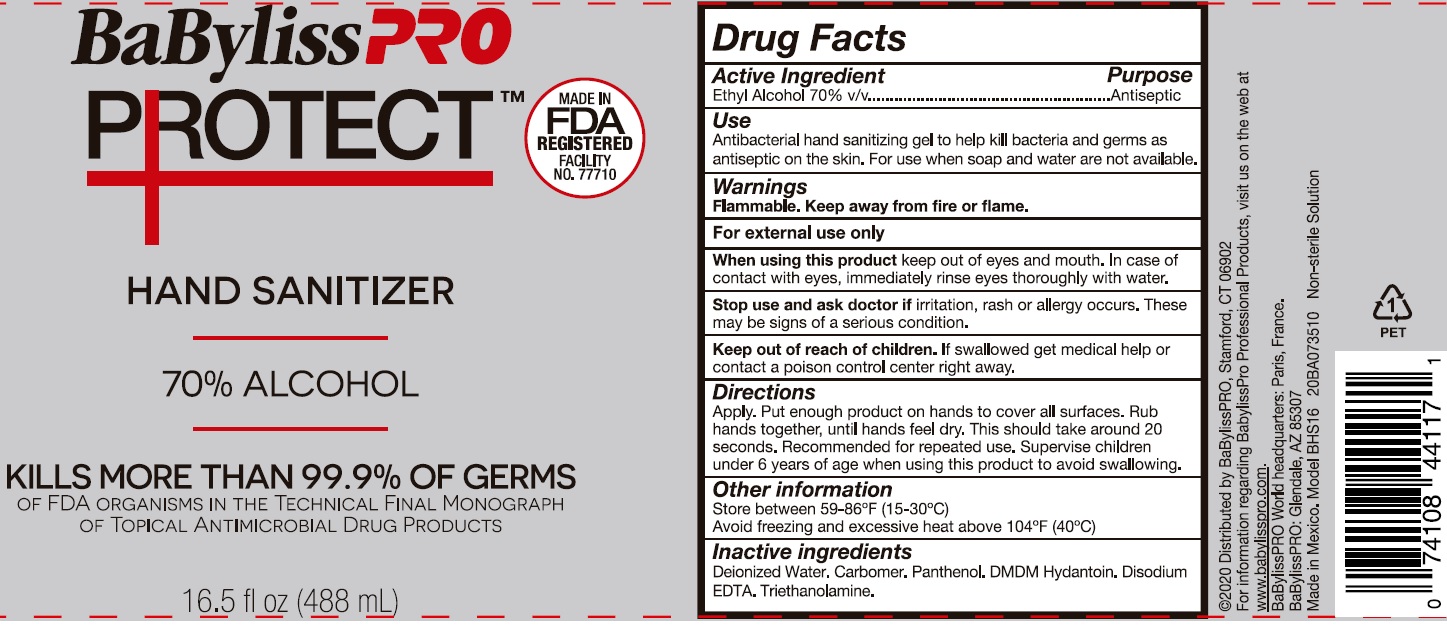 DRUG LABEL: BABYLISS PRO PROTECT HAND SANITIZER
NDC: 12829-0002 | Form: GEL
Manufacturer: Conair Corporation
Category: otc | Type: HUMAN OTC DRUG LABEL
Date: 20201022

ACTIVE INGREDIENTS: ALCOHOL 0.7 mL/1 mL
INACTIVE INGREDIENTS: WATER; CARBOMER HOMOPOLYMER, UNSPECIFIED TYPE; PANTHENOL; DMDM HYDANTOIN; EDETATE DISODIUM ANHYDROUS; TROLAMINE

BABYLISS PRO PROTECT HAND SANITIZER

Active Ingredient

Ethyl Alcohol 70% V/V

Purpose

Antiseptic

Use

Antibacterial hand sanitizing gel to help kill bacteria and germs as antiseptic on the skin. For use when soap and water are not available.

Warnings

Flammable. Keep away from fire or flame.

For external use only

When using this product

keep out of eyes and mouth. In case of contact with eyes, immediately rinse eyes thoroughly with water.

Stop use and ask doctor if

irritation, rash or allergy occurs. These may be signs of a serious condition.

Keep out of reach of children.

If swallowed get medical help or contact a poison control center right away.

Directions

Apply. Put enough product on hands to cover all surfaces. Rub hands together, until hands feel dry. This should take around 20 seconds. Recommended for repeated use. Supervise children under 6 years of age when using this product to avoid swallowing.

Other information

Store between 59-86°F (15-30°C)
Avoid freezing and excessive heat above 104°F (40°C)

Inactive ingredients

Deionized Water. Carbomer. Panthenol. DMDM Hydantoin. Disodium EDTA. Triethanolamine.